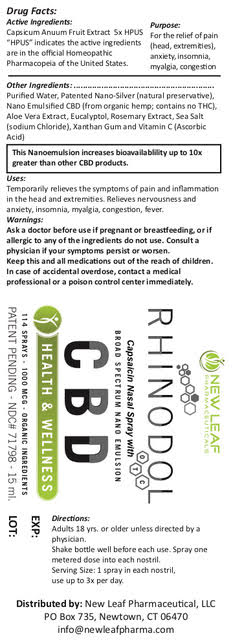 DRUG LABEL: Rhinodol
NDC: 71798-015 | Form: SPRAY
Manufacturer: New Leaf Pharmaceutical, LLC
Category: homeopathic | Type: HUMAN OTC DRUG LABEL
Date: 20190927

ACTIVE INGREDIENTS: CAPSICUM 5 [hp_X]/0.263 mL
INACTIVE INGREDIENTS: SILVER; XANTHAN GUM; ROSEMARY; ASCORBIC ACID; WATER; CANNABIS SATIVA SEED OIL; SEA SALT; ALOE; EUCALYPTOL

Rhinodol Nasal Spray

Active Ingredients:

Capsicum Anuum Fruit Extract 5x HPUS

"HPUS" indicates the active ingredients are in the official Homeopathic Pharmacopeia of the United States.

Purpose:

For the relief of pain (head, extremities), anxiety, insomnia, myalgia, congestion

Uses:

Temporarily relieves the symptoms of pain and inflammation in the head and extremities. Relieves nervousness and anxiety, insomnia, myalgia, congestion, fever.

Warnings:

As with any drug, ask a doctor before use if pregnant or breastfeeding, or if allergic to any of the ingredients do not use. Consult a physician if your symptoms persist or worsen.

DOSAGE AND ADMINISTRATION

Facts:

1 spray in each nostril (2 total sprays)

500 mcg

Sprays per container 114

Directions:

Adults 18 yrs. or older unless directed by physician.

Shake bottle well before each use. Spray one metered dose into each nostril.

Serving Size: 1 spray in each nostril

Use up to 3x per day.

INACTIVE INGREDIENT

Other Ingredients:

Purified water, Patented Nano-Silver (natural preservative), Nano Emulsified CBD (from organic hemp; contains no THC), Aloe Vera Extract, Eucalyptol, Rosemary Extract, Sea Salt (sodium chloride), Xanthan Gum and Vitamin C (Ascorbic Acid).

This Nanoemulsion increases bioavailability up to 10x greater than other CBD products.

KEEP OUT OF REACH OF CHILDREN

Keep this and all medications out of the reach of children. In case of accidental overdose, contact a medical professional or a poison control center immediately.